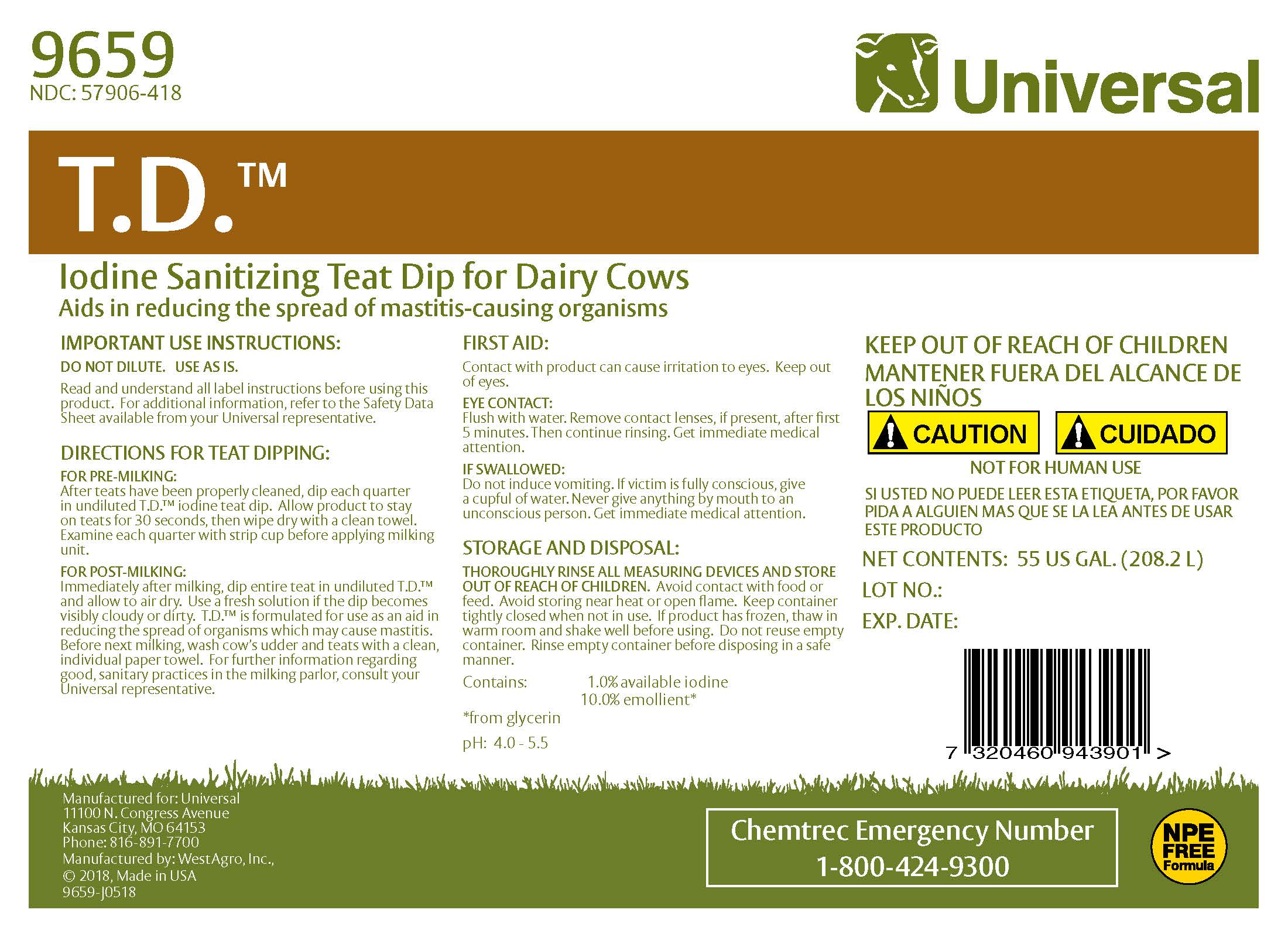 DRUG LABEL: T.D.
NDC: 57906-418 | Form: SOLUTION
Manufacturer: Universal
Category: animal | Type: OTC ANIMAL DRUG LABEL
Date: 20230216

ACTIVE INGREDIENTS: IODINE 11.0 g/1 L
INACTIVE INGREDIENTS: SODIUM HYDROXIDE; ANHYDROUS CITRIC ACID; GLYCERIN; XANTHAN GUM; POLOXAMER 335; SODIUM IODIDE; NONOXYNOL-12; WATER

Universal
T.D.
Iodine Sanitizing Teat Dip for Dairy Cows

9659

NDC: 57906-418

PURPOSE

Aids in reducing the spread of mastitis-causing organisms

IMPORTANT USE INSTRUCTIONS:

DO NOT DILUTE. USE AS IS.

Read and understand all label instructions before using this product. For additional information, refer to the Material Safety Data Sheet available from your Universal representative.

DIRECTIONS FOR TEAT DIPPING:

FOR PRE-MILKING:

After teats have been properly cleaned, dip each quarter in undiluted T.D. iodine teat dip. Allow product to stay on teats for 30 seconds, then wipe dry with a clean towel. Examine each quarter with strip cup before applying milking unit.

FOR POST-MILKING:

Immediately after milking, dip entire teat in undiluted T.D. and allow to air dry. Use a fresh solution if the dip becomes visibly cloudy or dirty. T.D. is formulated for use as an aid in reducing the spread of organisms which may cause mastitis. Before next milking, wash cow's udder and teats with a clean, individual paper towel. For further information regarding good, sanitary practices in the milking parlor, consult your Universal representative.

Manufactured for: Universal
11100 N. Congress Avenue
Kansas City, MO 64153
Phone: 816-891-7700
Manufactured by: WestAgro, Inc.
©2018, Made in USA

FIRST AID

Contact with product can cause irritation to eyes. Keep out of eyes.

EYE CONTACT:

Flush with water. Remove contact lenses if present, after first 5 minutes. Then continue rinsing. Get immediate medical attention.

IF SWALLOWED:

Do not induce vomiting. If victim is fully conscious, give a cupful of water. Never give anything by mouth to an unconscious person. Get immediate medical attention.

STORAGE AND DISPOSAL:

THOROUGHLY RINSE ALL MEASURING DEVICES AND STORE OUT OF REACH OF CHILDREN. Avoid contact with food or feed. Avoid storing near heat or open flame. Keep container tightly closed when not in use. If product has frozen, thaw in warm room and shake well before using. Do not reuse empty container. Rinse empty container before disposing in a safe manner.

ACTIVE INGREDIENT

Contains: 1.0% available iodine

10.0% emollient*

* from glycerin

pH: 4.0 - 5.5

Chemtrec Emergency Number

1-800-424-9300

KEEP OUT OF REACH OF CHILDREN

MANTENER FUERA DEL ALCANCE DE LOS NINOS

WARNINGS AND PRECAUTIONS

! CAUTION ! CUIDADO

NOT FOR HUMAN USE

SI USTED NO PUEDE LEER ESTA ETIQUETA, POR FAVOR PIDA A ALGUIEN MAS QUE SE LA LEA ANTES DE USAR ESTE PRODUCTO

SAFE HANDLING WARNING

HAZARD RATING

4 - EXTREME

3 - HIGH

2 - MODERATE

1 - SLIGHT

0 - INSIGNIFICANT

HEALTH 1

FIRE 0

INSTABILITY 1

SPECIAL NONE

Net Contents: US GAL. (LITERS)

Lot No.:

Exp. Date:

Chemtrec Emergency Number

1-800-424-9300

NPE FREE Formula